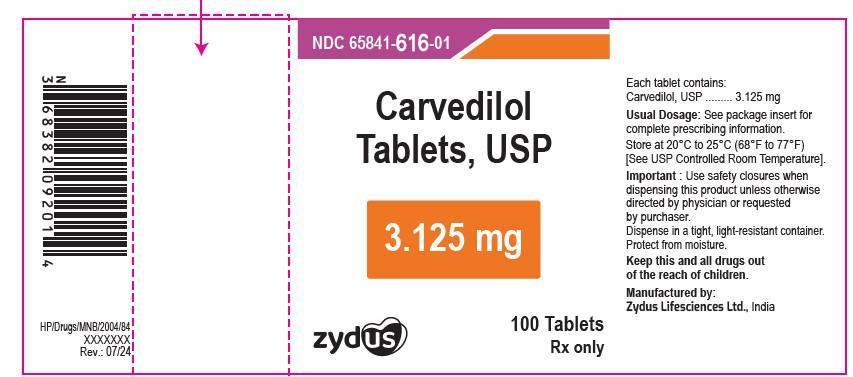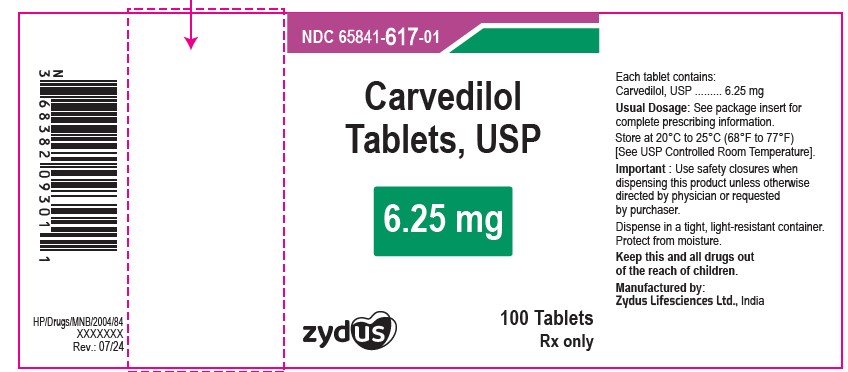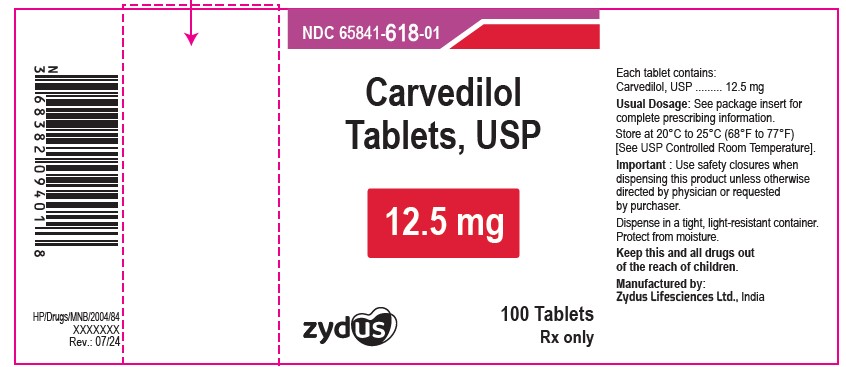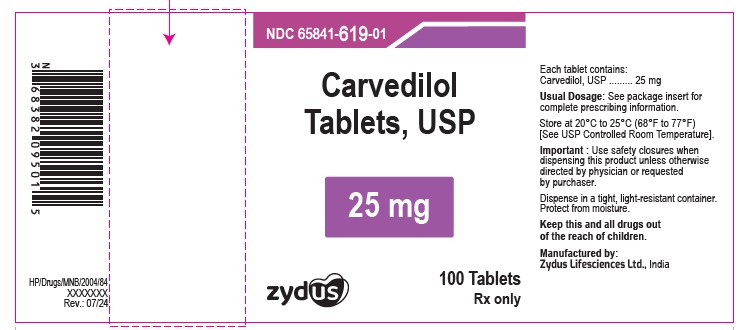 DRUG LABEL: Carvedilol
NDC: 65841-616 | Form: TABLET, FILM COATED
Manufacturer: Zydus Lifesciences Limited
Category: prescription | Type: HUMAN PRESCRIPTION DRUG LABEL
Date: 20251231

ACTIVE INGREDIENTS: CARVEDILOL 3.125 mg/1 1
INACTIVE INGREDIENTS: CROSPOVIDONE; HYPROMELLOSE, UNSPECIFIED; LACTOSE MONOHYDRATE; MAGNESIUM STEARATE; POLYETHYLENE GLYCOL, UNSPECIFIED; POVIDONE K30; SILICON DIOXIDE; TALC; TITANIUM DIOXIDE

CARVEDILOL TABLETS

PACKAGE LABEL.PRINCIPAL DISPLAY PANEL

NDC 65841-616-01 in bottle of 100 Tablets

Carvedilol Tablets USP, 3.125 mg

Rx only

100 Tablets

NDC 65841-617-01 in bottle of 100 Tablets

Carvedilol Tablets USP, 6.25 mg

Rx only

100 Tablets

NDC 65841-618-01 in bottle of 100 Tablets

Carvedilol Tablets USP, 12.5 mg

Rx only

100 Tablets

NDC 65841-619-01 in bottle of 100 Tablets

Carvedilol Tablets USP, 25 mg

Rx only

100 Tablets